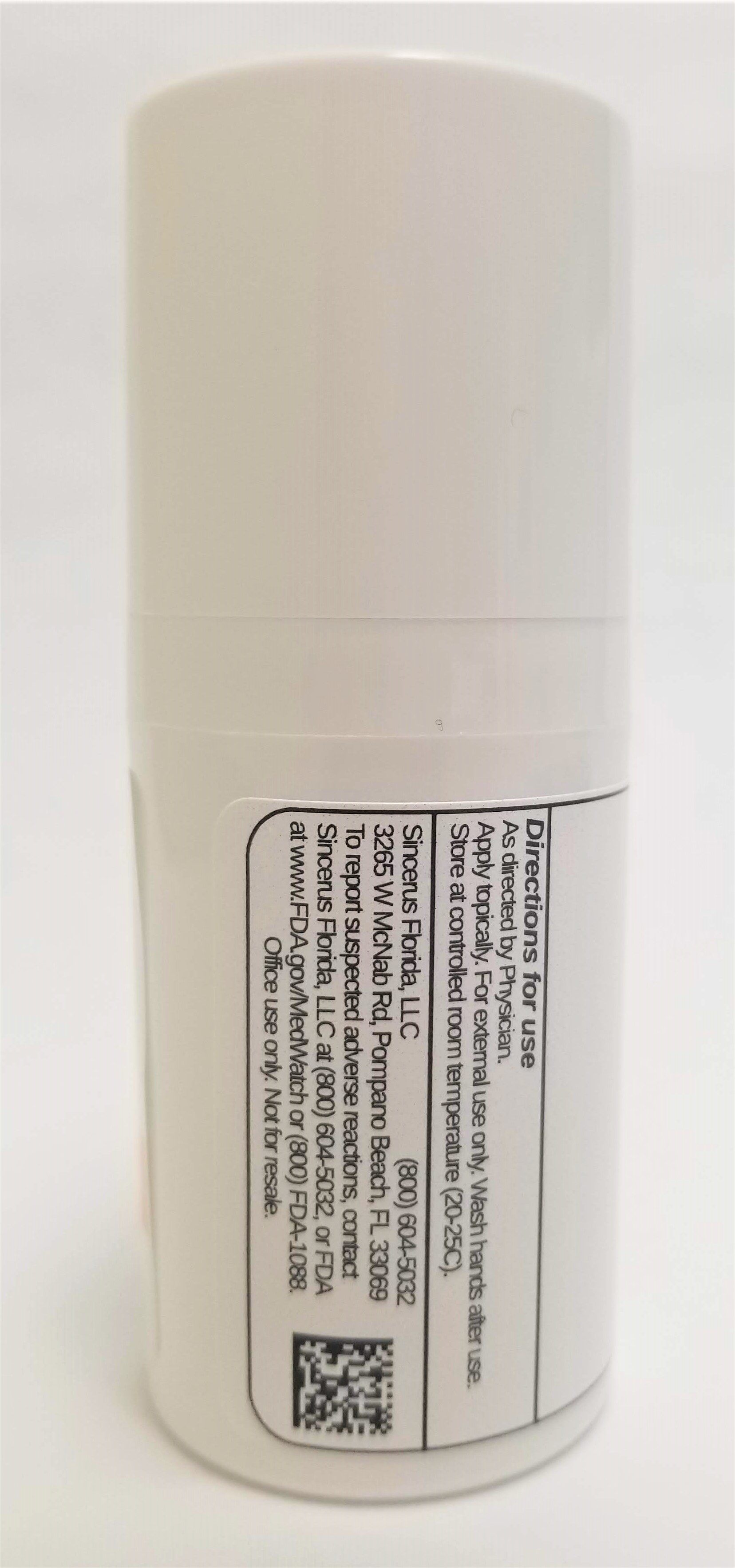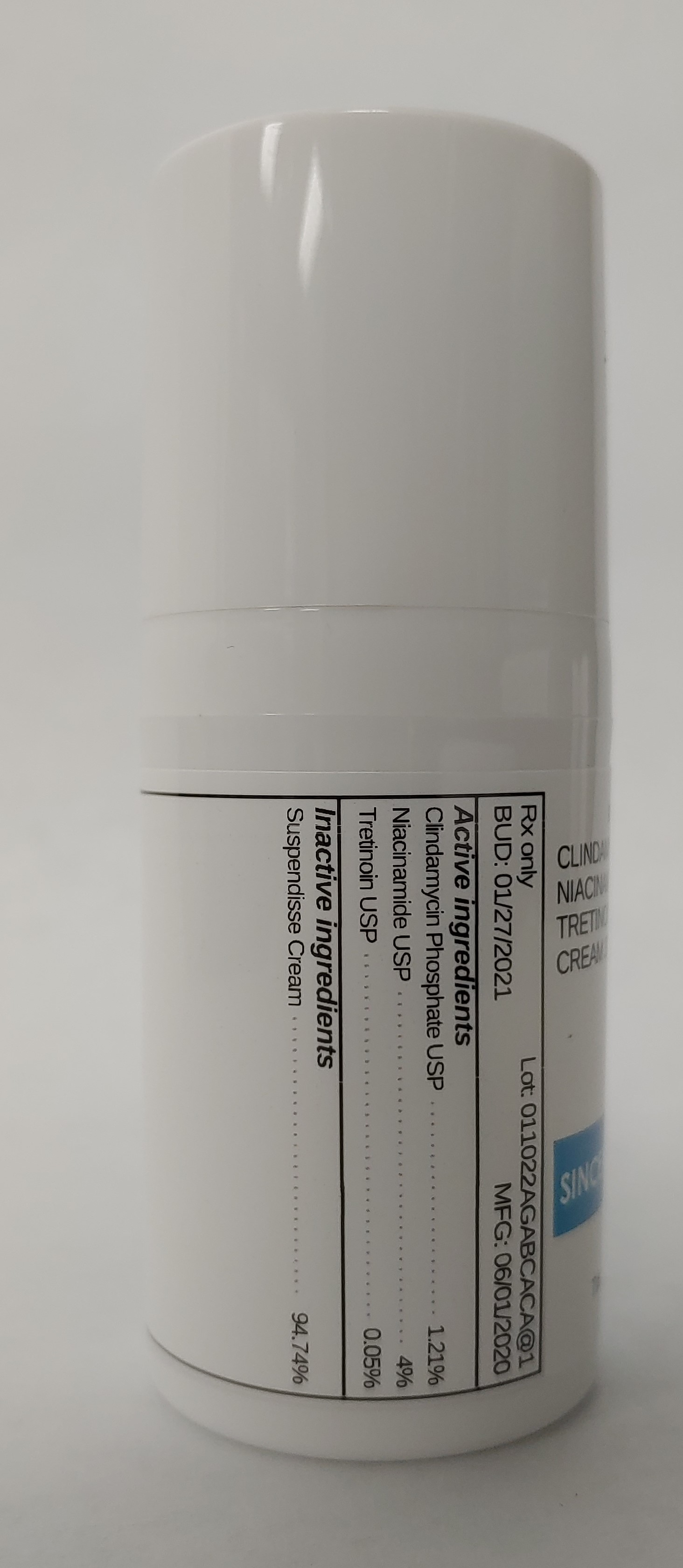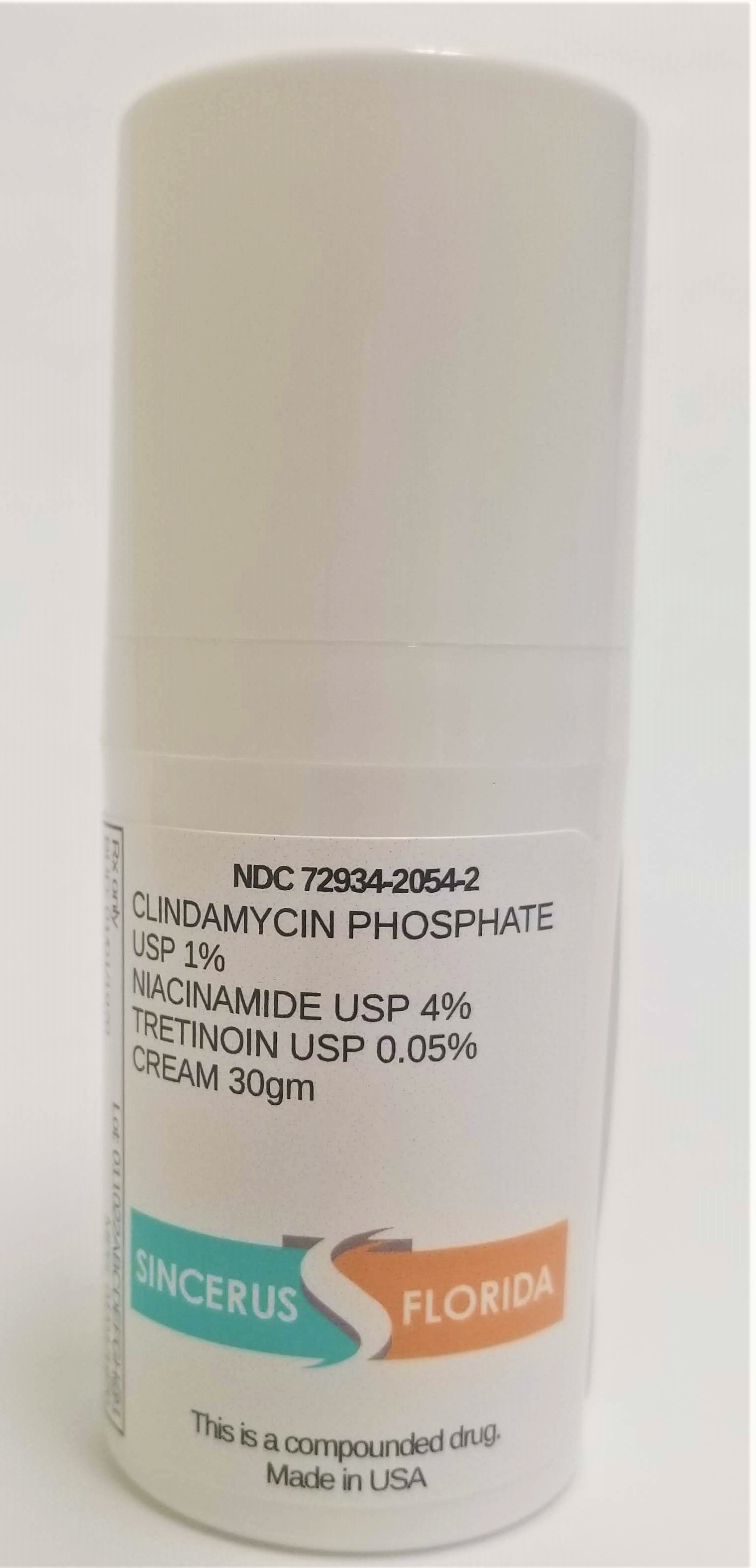 DRUG LABEL: CLINDAMYCIN 1% / NIACINAMIDE 4% / TRETINOIN 0.05%
NDC: 72934-2054 | Form: CREAM
Manufacturer: Sincerus Florida, LLC
Category: prescription | Type: HUMAN PRESCRIPTION DRUG LABEL
Date: 20200604

ACTIVE INGREDIENTS: NIACINAMIDE 4 g/100 g; CLINDAMYCIN PHOSPHATE 1 g/100 g; ALITRETINOIN 0.05 g/100 g

CLINDAMYCIN 1% / NIACINAMIDE 4% / TRETINOIN 0.05%